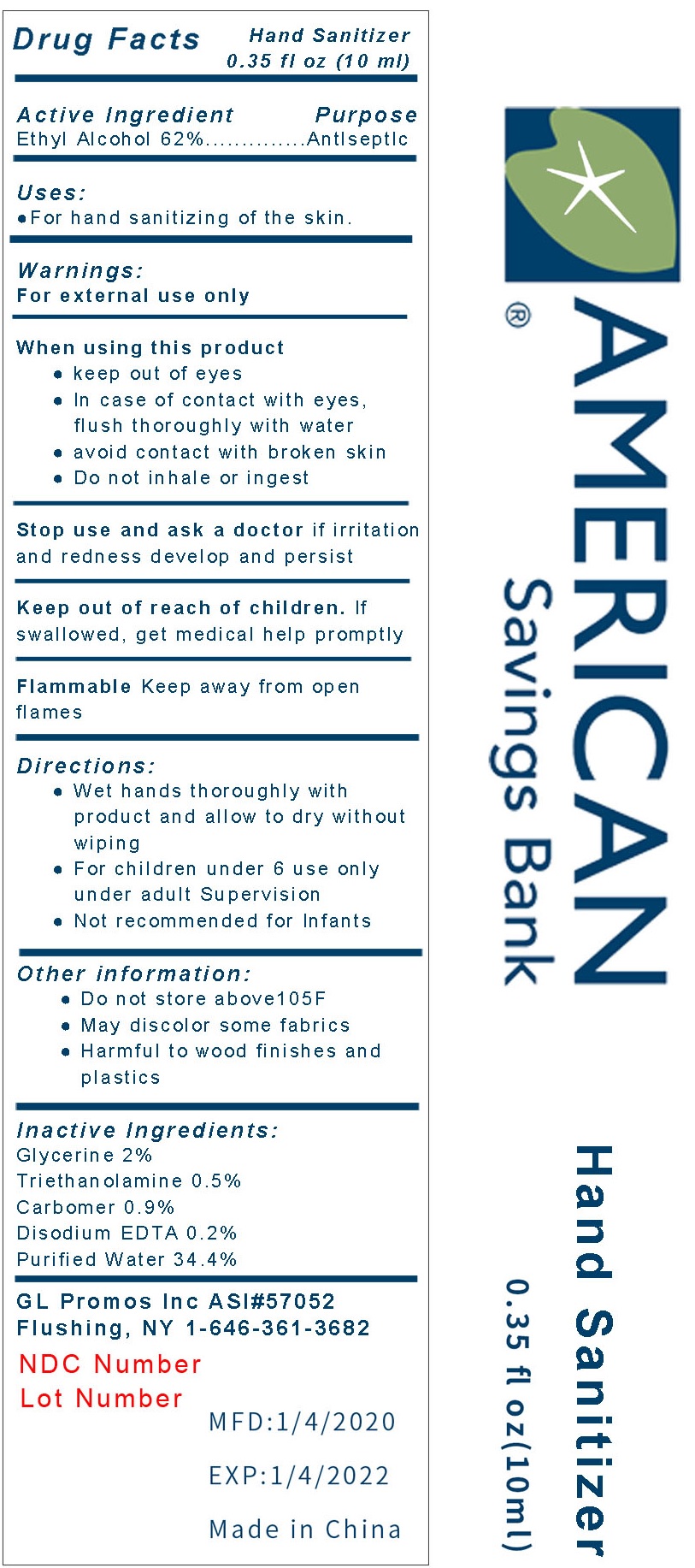 DRUG LABEL: American Savings Bank Hand Sanitizer
NDC: 71734-304 | Form: GEL
Manufacturer: JIANGMEN SHUIZIRUN SANITARY ARTICLES CO., LTD.
Category: otc | Type: HUMAN OTC DRUG LABEL
Date: 20200409

ACTIVE INGREDIENTS: ALCOHOL 62 mL/100 mL
INACTIVE INGREDIENTS: WATER; GLYCERIN; TROLAMINe; EDETATE DISODIUM

Active ingredient

62% Ethyl Alcohol

Purpose

Antiseptic

Use

For hand sanitizeing of the skin.

Warnings

For external use only.

Flammable, keep away from open flames.

When using this product

- keep out of eyes
- In case of contact with eyes, flush thoroughly with water
- Avoid contact with broken skin
- Do not inhale or ingest

Stop use and ask a doctor if irritation and redness develop and persist

Keep out of reach of children.

If swallowed, get medical help promptly.

Directions

- Wet hands thoroughly with product and allow to dry without wiping
- For children under 6 use only under adult supervision
- Not recommended for infants

Inactive ingredients

Glycerin 2%, Triethanolamine 0.5%, Carbomer 0.9%, Disodium EDTA 0.2%, Pure Water 34.4%

Other Information:

- Do not store above 105 ℉
- May discolor some fabrics
- Harmful to wood finishes and plastics